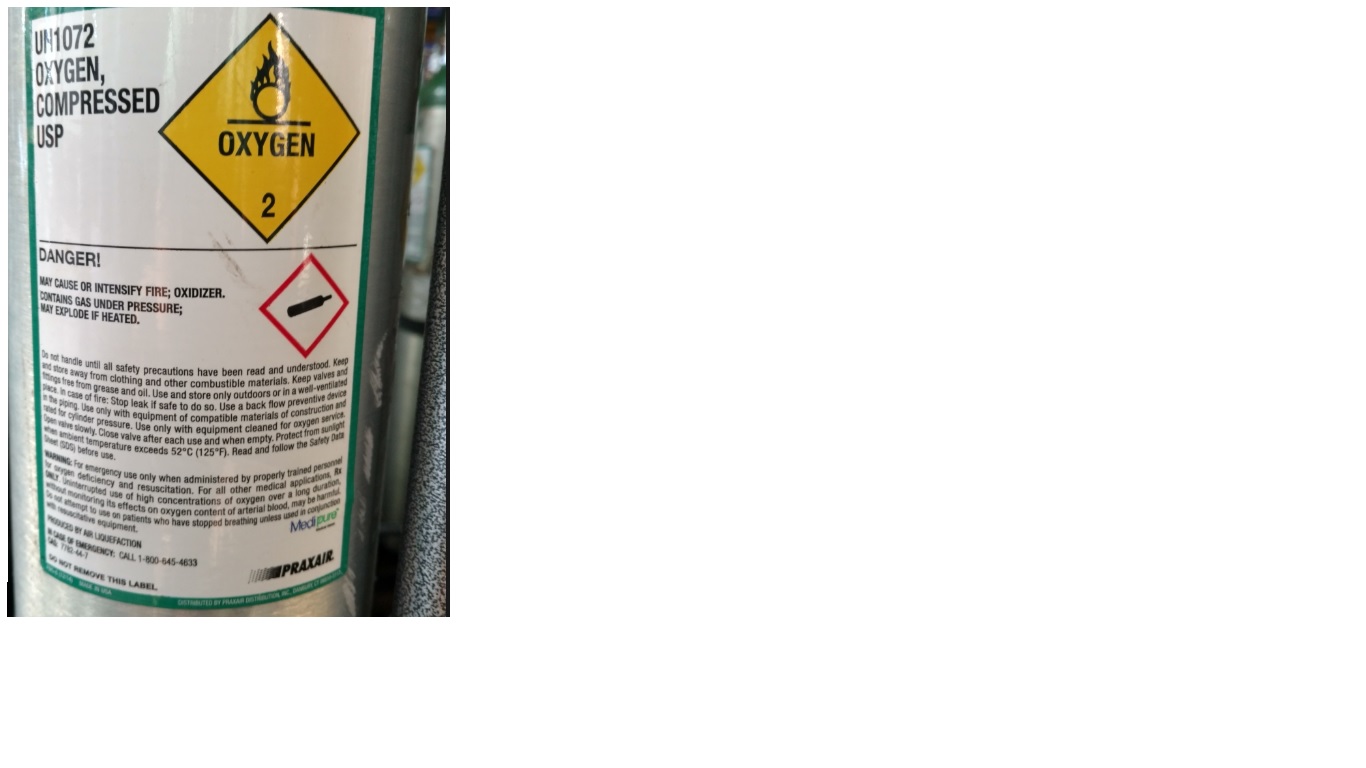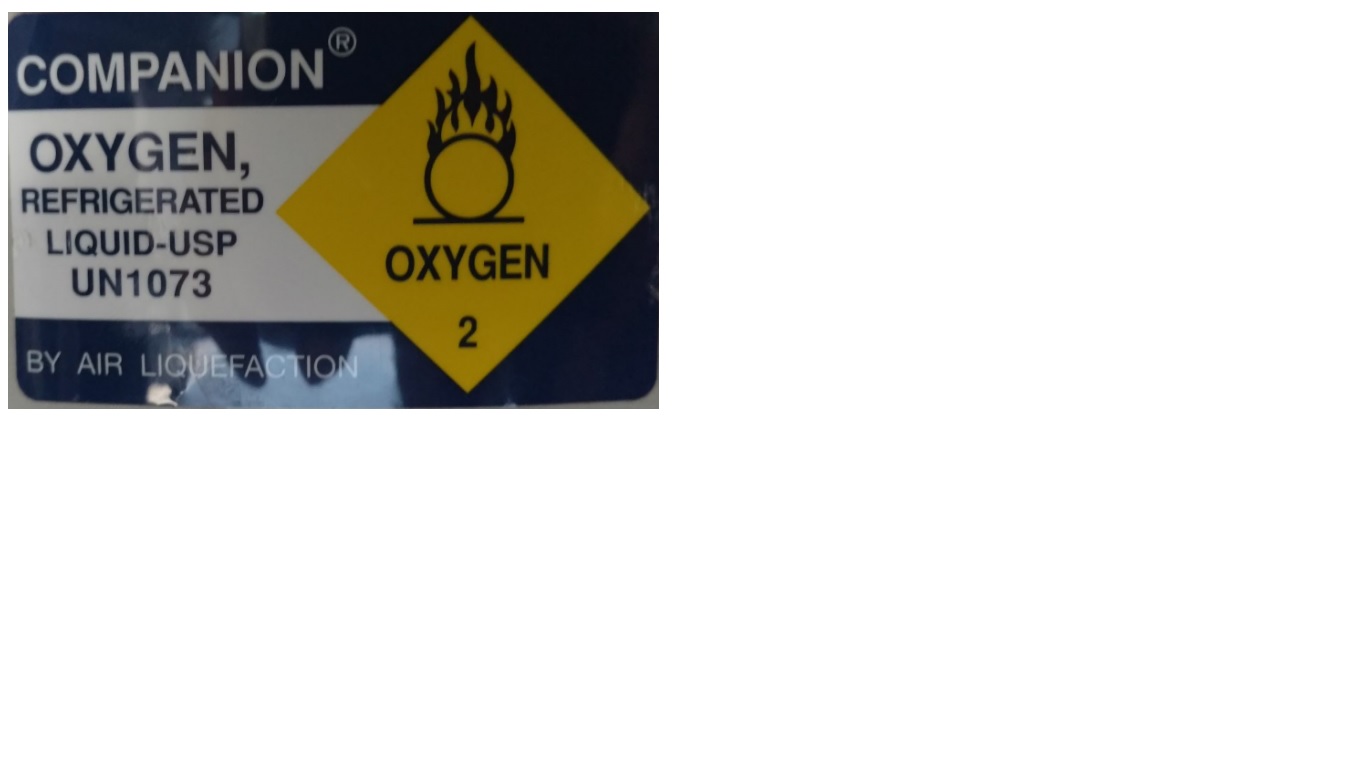 DRUG LABEL: Oxygen
NDC: 72231-001 | Form: GAS
Manufacturer: Belcrest Services, LTD.
Category: prescription | Type: HUMAN PRESCRIPTION DRUG LABEL
Date: 20191122

ACTIVE INGREDIENTS: OXYGEN 990 mL/1 L

Oxygen

PACKAGE LABEL

UN1072

OXYGEN, COMPRESSED USP

DANGER!

MAY CAUSE OR INTENSIFY FIRE; OXIDIZER.

CONTAINS GAS UNDER PRESSURE; MAY EXLPODE IF HEATED.

Do not handle until all safety precautions have been read and understood. Keep and store away from clothing and other combustible materials. Keep valves and fittings free from grease and oil. Use and store only outdoors or in a well-ventilated place. In case of fire: Stop leak if safe to do so. Use a back flow preventive device in the piping. Use only with equipment of compatible materials of construction and rated for cylinder pressure. Use only with equipment cleaned for oxygen service. Open valve slowly. Close valve after each use and when empty. Protect from sunlight when ambient temperature exceeds 52 C (125 F). Read and follow the Safety Data Sheet (SDS) before use.

WARNING: For emergency use only when administered by properly trained personnel for oxygen deficiency and resuscitation. For all other medical applications, Rx ONLY. Uninterrupted use of high concentrations of oxygen over a long duration, without monitoring its effects on oxygen content of arterial blood, may be harmful. Do not attempt to use on patients who have stopped breathing unless used in conjunction with resuscitative equipment. Medipure

PRODUCED BY AIR LIQUEFACTION

IN CASE OF EMERGENCY: CALL 1-800-645-4633

CAS: 7782-44-7

DO NOT REMOVE THIS LABEL.

PRAXAIR

MADE IN USA

DISTRIBUTED BY PRAXAIR DISTRIBUTION, INC., DANBURY, CT

PACKAGE LABEL

COMPANION

OXYGEN, REFRIGERATED LIQUID-USP

UN1073

BY AIR LIQUEFACTION